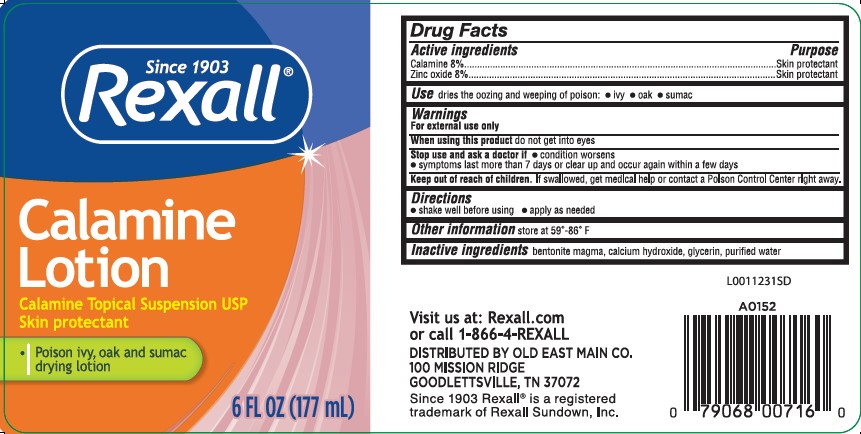 DRUG LABEL: Calamine
NDC: 55910-063 | Form: LOTION
Manufacturer: Old East Main Co.
Category: otc | Type: HUMAN OTC DRUG LABEL
Date: 20260302

ACTIVE INGREDIENTS: FERRIC OXIDE RED 80 mg/1 mL; ZINC OXIDE 80 mg/1 mL
INACTIVE INGREDIENTS: BENTONITE; CALCIUM HYDROXIDE; GLYCERIN; WATER

Rexall 063.001/063AA
Calamine Lotion

Active ingredients

Calamine 8%
Zinc oxide 8%

Purpose

Skin protectant

Use

dries the oozing and weeping of poison:

- ivy
- oak
- sumac

Warnings

For external use only

When using this product

do not get into eyes

Stop use and ask a doctor if

- condition worsens
- symptoms last more than 7 days or clear up and occur again within a few days

Keep out of reach of children.

If swallowed, get medical help or contact a Poison Control Center right away.

Directions

- shake well before using
- apply as needed

Other information

store at 59⁰ - 86⁰ F

Inactive ingredients

bentonite magma, calcium hydroxide, glycerin, purified water

ADVERSE REACTION

Visit us at: Rexall.com

or call 1-866-4REXALL
DISTRIBUTED BY OLD EAST MAIN CO.

100 MISSION RIDGE

GOODLETTSVILLE, TN 37072

Since 1903 Rexallis a registered trademark of Rexall Sundown, Inc.

principal display panel

Since 1903
REXALL®

Calamine Lotion
Calamine Topical Suspension USP

Skin Protectant
• Poison ivy, oak and sumac drying lotion

6 FL OZ (177 mL)